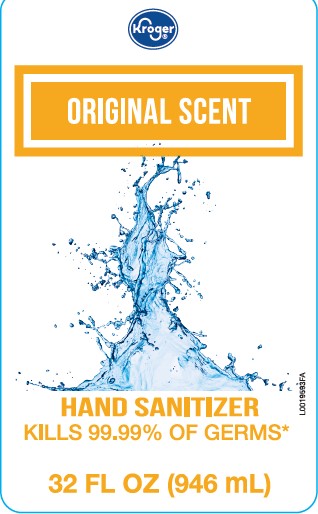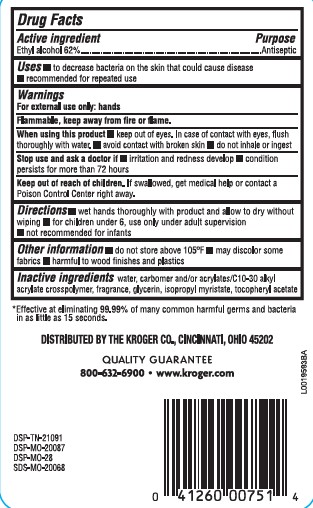 DRUG LABEL: Alcohol
NDC: 30142-849 | Form: LIQUID
Manufacturer: The Kroger Co.
Category: otc | Type: HUMAN OTC DRUG LABEL
Date: 20260227

ACTIVE INGREDIENTS: ALCOHOL 62 mL/100 mL
INACTIVE INGREDIENTS: CARBOMER HOMOPOLYMER, UNSPECIFIED TYPE; CARBOMER INTERPOLYMER TYPE A (ALLYL SUCROSE CROSSLINKED); GLYCERIN; ISOPROPYL MYRISTATE; TOCOPHEROL; WATER

Kroger 849.001/849AA-AF, BA
Moisturizing Hand Sanitizer

Active ingredient

Ethyl Alcohol 62%

Purpose

Antiseptic

Uses

- to decrease bacteria on the skin that could cause disease
- recommended for repeated use

Warnings

For exterenal use only-hands

Flammable, keep away from fire or flame.

When using this product

- keep out of eyes. In case of contact with eyes, flush thoroughly with water.
- avoid contact with broken skin
- do not inhale or ingest

Stop use and ask a doctor if

- irritation and redness develop
- condition persists for more than 72 hours

Keep out of reach of children.

If swallowed, get medical help or contact a Poison Control Center right away.

Directions

- wet hands thoroughly with product and allow to dry without wiping
- for children under 6, use only under adult supervision
- not recommended for infants

Other information

- do not store above 105⁰F
- may discolor some fabrics
- harmful to wood finishes and plastics

Inactive ingredients

water, carbomer and/or acrylates/C10-30 alkyl acrylate crosspolymer, fragrance, glycerin, isopropyl myristate, tocopheryl acetate

ADVERSE REACTION

*Effective at eliminating 99.99% of many common harmful germs and bacteria in as little as 15 seconds.

DISTRIBUTED BY THE KROGER CO., CINCINNATI, OHIO 45202

QUALITY GUARANTEE

800-362-6900 www.kroger.com

DSP-TN-21091

DSP-MO-20087

DSP-MO-28

SDS-MO-20068

principal display panel

Kroger®

ORIGINAL SCENT

HAND SANITIZER

KILLS 99.99% OF GERMS*

32 FL OZ (946 mL)